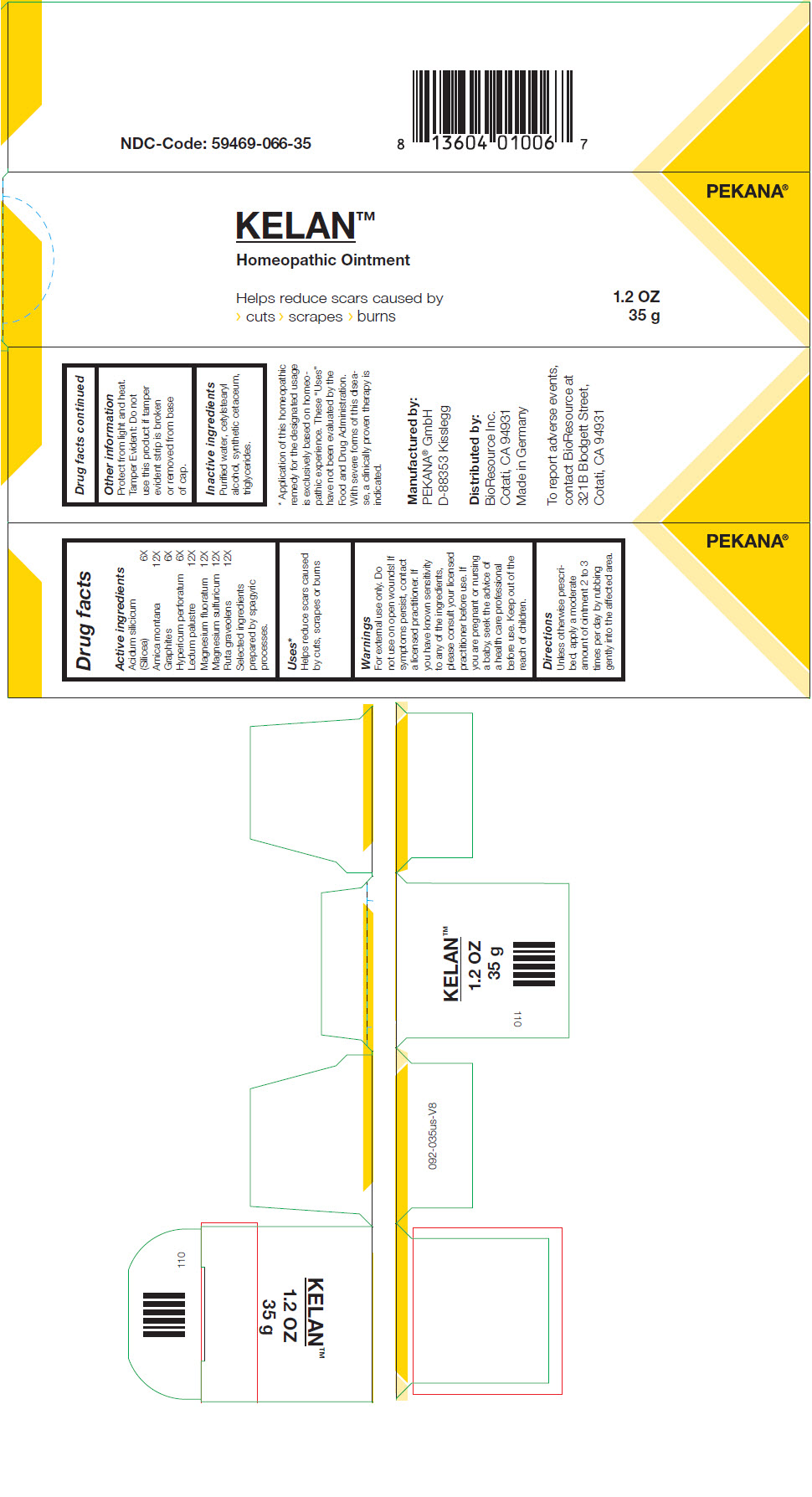 DRUG LABEL: KELAN
NDC: 59469-066 | Form: OINTMENT
Manufacturer: PEKANA Naturheilmittel GmbH
Category: homeopathic | Type: HUMAN OTC DRUG LABEL
Date: 20221222

ACTIVE INGREDIENTS: Silicon Dioxide 6 [hp_X]/35 g; Arnica montana Root 12 [hp_X]/35 g; Graphite 6 [hp_X]/35 g; HYPERICUM PERFORATUM WHOLE 6 [hp_X]/35 g; RHODODENDRON TOMENTOSUM LEAFY TWIG 12 [hp_X]/35 g; Magnesium fluoride 12 [hp_X]/35 g; Magnesium sulfate heptahydrate 12 [hp_X]/35 g; Ruta graveolens Flowering Top 12 [hp_X]/35 g
INACTIVE INGREDIENTS: Medium-Chain Triglycerides; Cetostearyl Alcohol; Cetyl Alcohol; Spermaceti; Water; Alcohol

KELAN™

Drug facts

Active ingredients
Acidum silicicum (Silicea) | 6X
Arnica montana | 12X
Graphites | 6X
Hypericum perforatum | 6X
Ledum palustre | 12X
Magnesium fluoratum | 12X
Magnesium sulfuricum | 12X
Ruta graveolens | 12X
Selected ingredients prepared by spagyric processes.

Uses [Application of this homeopathic remedy for the designated usage is exclusively based on homeopathic experience. These "Uses" have not been evaluated by the Food and Drug Administration. With severe forms of this disease, a clinically proven therapy is indicated.]

PURPOSE

Helps reduce scars caused by cuts, scrapes or burns

Warnings

For external use only. Do not use on open wounds! If symptoms persist, contact a licensed practitioner. If you have known sensitivity to any of the ingredients, please consult your licensed practitioner before use. If you are pregnant or nursing a baby, seek the advice of a health care professional before use.

Keep out of the reach of children.

Directions

Unless otherwise prescribed, apply a moderate amount of ointment 2 to 3 times per day by rubbing gently into the affected area.

Other information

Protect from light and heat.

Tamper Evident

Do not use this product if tamper evident strip is broken or removed from base of cap.

Inactive ingredients

Purified water, cetylstearyl alcohol, synthetic cetaceum, triglycerides.

Manufactured by:
PEKANA® GmbH
D-88353 Kisslegg

Distributed by:
BioResource Inc.
Cotati, CA 94931
Made in Germany

PRINCIPAL DISPLAY PANEL - 35 g Tube Box

PEKANA®

KELAN™
Homeopathic Ointment

Helps reduce scars caused by
> cuts > scrapes > burns

1.2 OZ
35 g